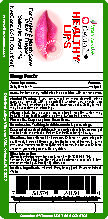 DRUG LABEL: Healthy Lips
NDC: 69469-012 | Form: SOLUTION/ DROPS
Manufacturer: VitaMex USA, Corp
Category: otc | Type: HUMAN OTC DRUG LABEL
Date: 20241115

ACTIVE INGREDIENTS: SALICYLIC ACID 10 mg/1 mL
INACTIVE INGREDIENTS: PROPYLENE GLYCOL; WATER; ALCOHOL; RHUBARB

Healthy Lips 0.5oz

Active Ingredient

Active Ingredient: Purpose:

Salicylic Acid 1%..........................Analgesic

Uses:

Uses: For temporary relief of pain associated with cancker sores.

Alcohol Warning:

Alcohol Warning: If you consume 3 or more alcoholic drinks everyday, consult with a specialist whether you should use Salicylic Acid or other pain reliver, fever reducers, Salicylic Acid may cause stomach bleeding.

Allergy Alert

Allergy Alert: May cause a sever allergic reaction which may include: hives, facial swelling, asthma (wheezing), shock.

Flammable

Flammable: Keep away from fire or flame.

Do not use for: Teething, in children under 2 years of age

Keep out of reach of children: Incase of accidental overdose, get medical help or contact a Poison Control Center right away.

Directions

Directions: Use child resistant dropper. children 14 years of age to adult. Apply 2 drops 2 times a day to affected area of the mouth, gums or mucous membranes (throat). Do not rinse mouth after use. Children under 14 years of age consult a physician.

Directions

Directions: Use child resistant dropper. children 14 years of age to adult. Apply 2 drops 2 times a day to affected area of the mouth, gums or mucous membranes (throat). Do not rinse mouth after use. Children under 14 years of age consult a physician.

Other Information

Store at controlled room temperature: 15-30°C (15-86°F).

Tamper Evident Feature: Do not use if cello-band over cap is torn, brocken or missing. Close tightly after use.

Inactive ingredients

Inactive ingredients: Alcohol, Propylene glycol, Rhubarb Extract, Water

Healthy Lips

Vita Mex USA

Dentarin

Healthy Lips

For Cancker & Mouth Sores

(Aftas & Fuegos)

Salicylic Acid 1%

Net Cont. 0.5fl os (15mL)